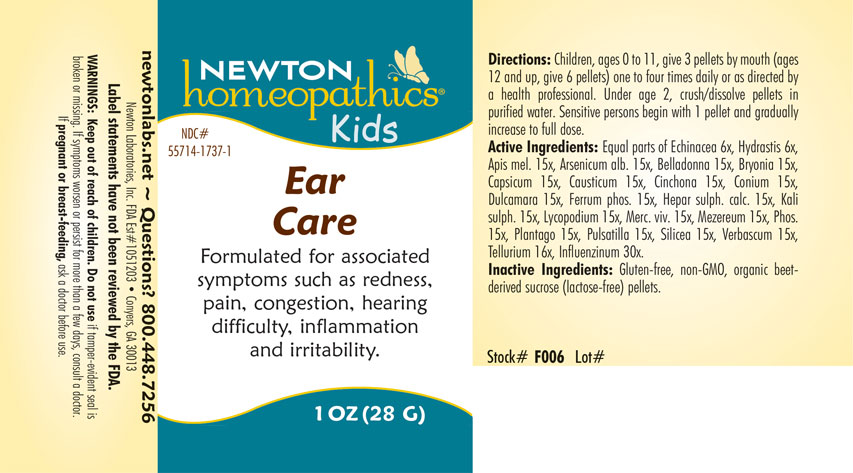 DRUG LABEL: Ear Care
NDC: 55714-1737 | Form: PELLET
Manufacturer: Newton Laboratories, Inc.
Category: homeopathic | Type: HUMAN OTC DRUG LABEL
Date: 20220318

ACTIVE INGREDIENTS: INFLUENZA B VIRUS 30 [hp_X]/1 g; ECHINACEA, UNSPECIFIED 6 [hp_X]/1 g; FERROSOFERRIC PHOSPHATE 15 [hp_X]/1 g; APIS MELLIFERA 15 [hp_X]/1 g; ARSENIC TRIOXIDE 15 [hp_X]/1 g; ATROPA BELLADONNA 15 [hp_X]/1 g; BRYONIA ALBA ROOT 15 [hp_X]/1 g; CAPSICUM 15 [hp_X]/1 g; CAUSTICUM 15 [hp_X]/1 g; CINCHONA OFFICINALIS BARK 15 [hp_X]/1 g; CONIUM MACULATUM FLOWERING TOP 15 [hp_X]/1 g; SOLANUM DULCAMARA TOP 15 [hp_X]/1 g; POTASSIUM SULFATE 15 [hp_X]/1 g; LYCOPODIUM CLAVATUM SPORE 15 [hp_X]/1 g; MERCURY 15 [hp_X]/1 g; DAPHNE MEZEREUM BARK 15 [hp_X]/1 g; PHOSPHORUS 15 [hp_X]/1 g; SILICON DIOXIDE 15 [hp_X]/1 g; PLANTAGO MAJOR 15 [hp_X]/1 g; ANEMONE PULSATILLA 15 [hp_X]/1 g; TELLURIUM 16 [hp_X]/1 g; VERBASCUM THAPSUS 15 [hp_X]/1 g; INFLUENZA A VIRUS 30 [hp_X]/1 g; CALCIUM SULFIDE 15 [hp_X]/1 g; GOLDENSEAL 6 [hp_X]/1 g
INACTIVE INGREDIENTS: SUCROSE

Ear 1737P

INDICATIONS AND USAGE SECTION

Formulated for associated symptoms such as redness, pain, congestion, hearing difficulty, inflammation and irritability.

DOSAGE & ADMINISTRATION SECTION

Directions: Children, ages 0 to 11, give 3 pellets by mouth (ages 12 and up, give 6 pellets) one to four times daily or a directed by a health professional. Under age 2, crush/dissolve pellets in purified water. Sensitive person begin with 1 pellet and gradually increase to full dose.

OTC - ACTIVE INGREDIENT SECTION

Equal parts of Echinacea 6x, Hydrastis canadensis 6x, Apis mellifica 15x, Arsenicum album 15x, Belladonna 15x, Bryonia 15x, Capsicum annuum 15x, Causticum 15x, Cinchona officinalis 15x, Conium maculatum 15x, Dulcamara 15x, Ferrum phosphoricum 15x, Hepar sulphuris calcareum 15x, Kali sulphuricum 15x, Lycopodium clavatum 15x, Mercurius vivus 15x, Mezereum 15x, Phosphorus 15x, Plantago major 15x, Pulsatilla 15x, Silicea 15x, Tellurium metallicum 16x, Verbascum thapsus 15x, Influenzinum 30x.

OTC - PURPOSE SECTION

Formulated for associated symptoms such as redness, pain, congestion, hearing difficulty, inflammation and irritability.

INACTIVE INGREDIENT SECTION

Gluten-free, non-GMO, organic beet-derived sucrose (lactose-free) pellets.

QUESTIONS SECTION

newtonlabs.net – Questions? 800.448.7256

Newton Laboratories, Inc. FDA Est # 1051203 - Conyers, GA 30013

WARNINGS SECTION

WARNINGS: Keep out of reach of children. Do not use if tamper-evident seal is broken or missing. If symptoms worsen or persist for more than a few days, consult a doctor. If pregnant or breast-feeding, ask a doctor before use.

OTC - PREGNANCY OR BREAST FEEDING SECTION

If pregnant or breast-feeding, ask a doctor before use.

OTC - KEEP OUT OF REACH OF CHILDREN SECTION

WARNINGS: Keep out of reach of children.